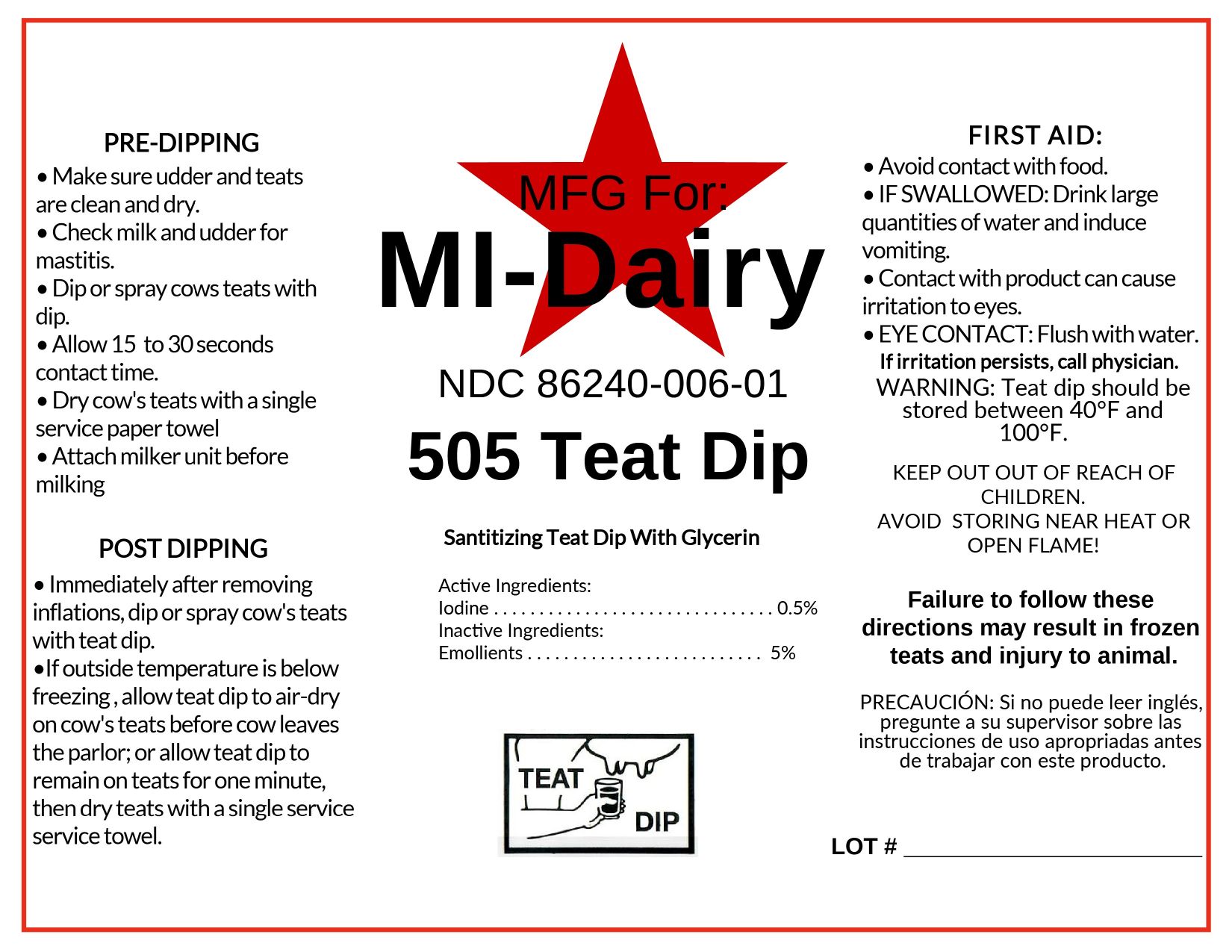 DRUG LABEL: 505 Teat Dip
NDC: 86240-006 | Form: SOLUTION
Manufacturer: Star City IBA, Inc.
Category: animal | Type: OTC ANIMAL DRUG LABEL
Date: 20250912

ACTIVE INGREDIENTS: IODINE 5 g/1 L
INACTIVE INGREDIENTS: SURFACTIN; GLYCERIN; SODIUM HYDROXIDE; WATER

MI-DAIRY
505 Teat Dip

Active Ingredients:

Iodine............................0.5%

PURPOSE

Sanitizing Teat Dip With Glycerin

INDICATIONS AND USAGE

PRE-DIPPING

- Make sure udder and teats are clean and dry.
- Check milk and udder for mastitis.
- Dip or spray cows teats with dip.
- Allow 15 to 30 seconds contact time.
- Dry cow's teats with a single service paper towel
- Attach milker unit before milking

POST DIPPING

- Immediately after removing inflations, dip or spray cow's teats with teat dip.
- If outside temperature is below freezing, allow teat dip to air-dry on cow's teats before cow leaves the parlor; or allow teat dip to remain on teats for one minute, then dry teats with a single service towel.

FIRST AID:

- Avoid contact with food.

- IF SWALLOWED: Drink large quantities of water and induce vomiting.

- Contact with product can cause irritation to eyes.

- EYE CONTACT: Flush with water. If irritation persists, call physician.

WARNINGS

WARNING: Teat dip should be stored between 40°F and 100°F.

KEEP OUT OF REACH OF CHILDREN.

AVOID STORING NEAR HEAT OR OPEN FLAME!

Inactive ingredients:

Emollients.........................5%